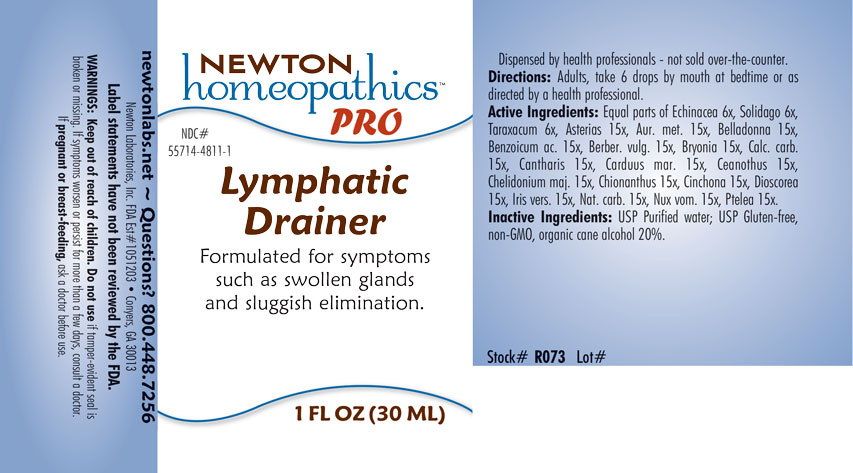 DRUG LABEL: Lymphatic Drainer
NDC: 55714-4811 | Form: LIQUID
Manufacturer: Newton Laboratories, Inc.
Category: homeopathic | Type: HUMAN OTC DRUG LABEL
Date: 20201204

ACTIVE INGREDIENTS: CINCHONA OFFICINALIS BARK 15 [hp_X]/1 mL; DIOSCOREA VILLOSA TUBER 15 [hp_X]/1 mL; IRIS VERSICOLOR ROOT 15 [hp_X]/1 mL; SODIUM CARBONATE 15 [hp_X]/1 mL; STRYCHNOS NUX-VOMICA SEED 15 [hp_X]/1 mL; PTELEA TRIFOLIATA BARK 15 [hp_X]/1 mL; ECHINACEA, UNSPECIFIED 6 [hp_X]/1 mL; TARAXACUM OFFICINALE 6 [hp_X]/1 mL; SOLIDAGO VIRGAUREA FLOWERING TOP 6 [hp_X]/1 mL; GOLD 15 [hp_X]/1 mL; BENZOIC ACID 15 [hp_X]/1 mL; MILK THISTLE 15 [hp_X]/1 mL; CEANOTHUS AMERICANUS LEAF 15 [hp_X]/1 mL; CHELIDONIUM MAJUS 15 [hp_X]/1 mL; BERBERIS VULGARIS ROOT BARK 15 [hp_X]/1 mL; LYTTA VESICATORIA 15 [hp_X]/1 mL; OYSTER SHELL CALCIUM CARBONATE, CRUDE 15 [hp_X]/1 mL; ATROPA BELLADONNA 15 [hp_X]/1 mL; BRYONIA ALBA ROOT 15 [hp_X]/1 mL; ASTERIAS RUBENS 15 [hp_X]/1 mL; CHIONANTHUS VIRGINICUS BARK 15 [hp_X]/1 mL
INACTIVE INGREDIENTS: WATER; ALCOHOL

Lymphatic 4811L

INDICATIONS & USAGE SECTION

Formulated for symptoms such as swollen glands and sluggish elimination.

DOSAGE & ADMINISTRATION SECTION

Directions: Adults, take 6 drops by mouth at bedtime or as directed by a health professional.

OTC - ACTIVE INGREDIENT SECTION

Equal parts of Echinacea 6x, Solidago 6x, Taraxacum 6x, Asterias 15x, Aur. met. 15x, Belladonna 15x, Benzoicum ac. 15x, Berber. vulg. 15x, Bryonia 15x, Calc. carb. 15x, Cantharis 15x, Carduus mar. 15x, Ceanothus 15x, Chelidonium maj. 15x, Chionanthus 15x, Cinchona 15x, Dioscorea 15x, Iris vers. 15x, Nat. carb. 15x, Nux vom. 15x, Ptelea 15x.

OTC - PURPOSE SECTION

Formulated for symptoms such as swollen glands and sluggish elimination.

INACTIVE INGREDIENT SECTION

I nactive Ingredients: USP Purified water; USP Gluten-free, non-GMO, organic cane alcohol 20%.

QUESTIONS SECTION

newtonlabs.net - Questions? 800.448.7256

Newton Laboratories, Inc. FDA Est # 1051203 Conyers, GA 30013

WARNINGS SECTION

WARNINGS: Keep out of reach of children. Do not use if tamper-evident seal is broken or missing. If symptoms worsen or persist for more than a few days, consult a doctor. If pregnant or breast-feeding, ask a doctor before use.

OTC - PREGNANCY OR BREAST FEEDING SECTION

If pregnant or breast-feeding, ask a doctor before use.

OTC - KEEP OUT OF REACH OF CHILDREN

Keep out of reach of children.